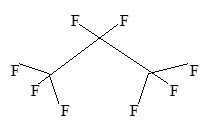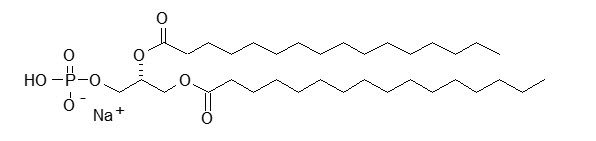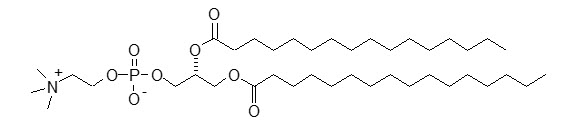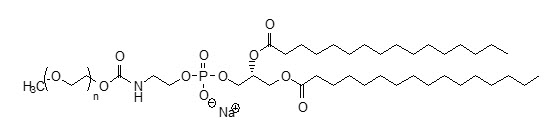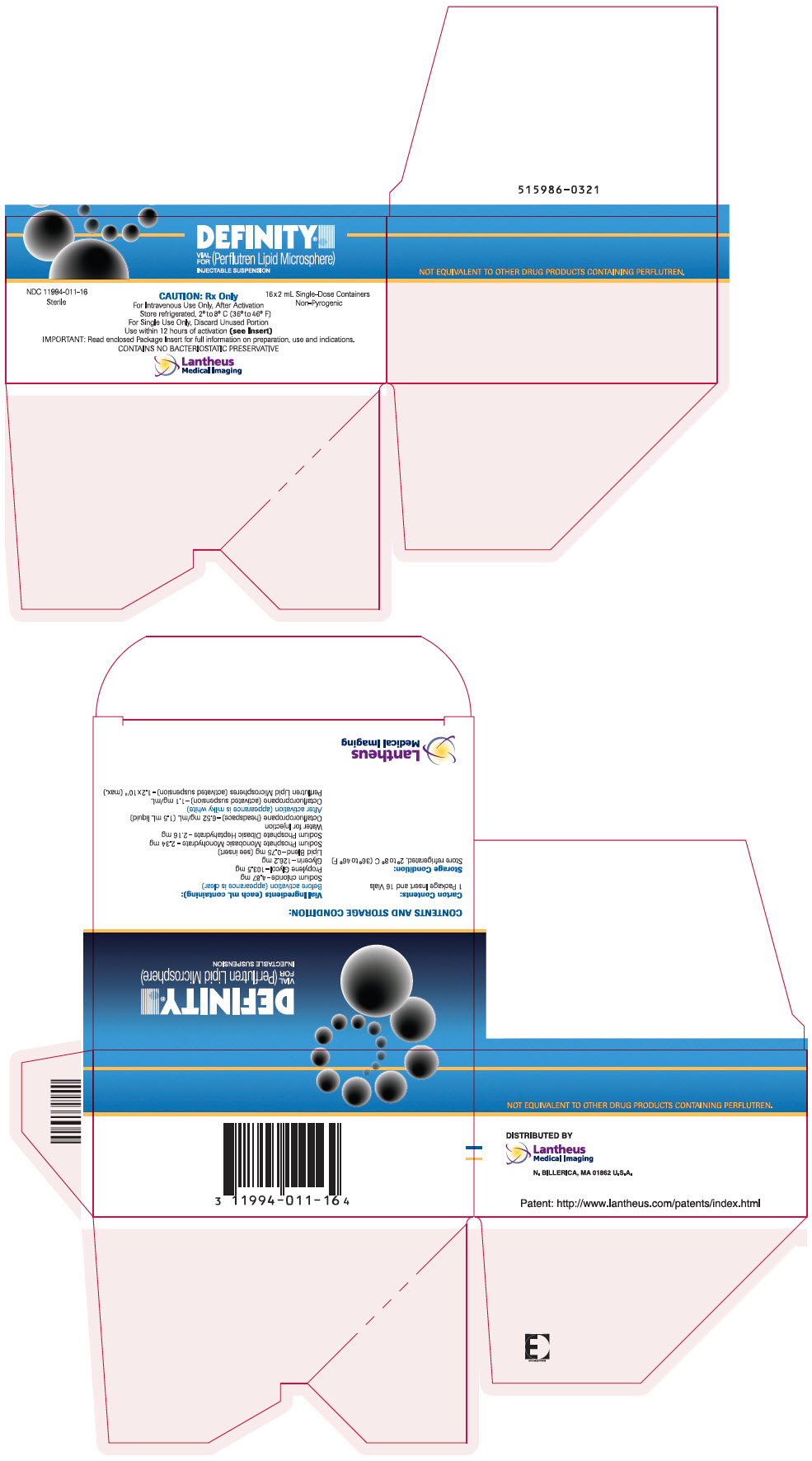 DRUG LABEL: Definity
NDC: 11994-011 | Form: INJECTION, SUSPENSION
Manufacturer: Lantheus Medical Imaging, Inc.
Category: prescription | Type: HUMAN PRESCRIPTION DRUG LABEL
Date: 20240313

ACTIVE INGREDIENTS: PERFLUTREN 6.52 mg/1 mL
INACTIVE INGREDIENTS: PROPYLENE GLYCOL 103.5 mg/1 mL; GLYCERIN 126.2 mg/1 mL; SODIUM CHLORIDE 4.87 mg/1 mL; SODIUM PHOSPHATE, MONOBASIC, MONOHYDRATE 2.34 mg/1 mL; SODIUM PHOSPHATE, DIBASIC, HEPTAHYDRATE 2.16 mg/1 mL

HIGHLIGHTS OF PRESCRIBING INFORMATION

These highlights do not include all the information needed to use DEFINITY safely and effectively. See full prescribing information for DEFINITY.
DEFINITY (perflutren lipid microsphere) injectable suspension, for intravenous use
Initial U.S. Approval: 2001

WARNING: SERIOUS CARDIOPULMONARY REACTIONS

Serious cardiopulmonary reactions, including fatalities, have occurred uncommonly during or following perflutren-containing microsphere administration. Most serious reactions occur within 30 minutes of administration.

- Assess all patients for the presence of any condition that precludes DEFINITY administration (4).
- Always have resuscitation equipment and trained personnel readily available(5.1) .

RECENT MAJOR CHANGES

Indications and Usage (1) | 3/2024
Dosage and Administration (2.1,2.3,2.4) | 3/2024
Warnings and Precautions, Pain Episodes in Patients with Sickle Cell Disease (5.5) | 6/2023

1 INDICATIONS AND USAGE

DEFINITY is an ultrasound contrast agent indicated, after activation, for use in adult and pediatric patients with suboptimal echocardiograms to opacify the left ventricular chamber and to improve the delineation of the left ventricular endocardial border. (1)

2 DOSAGE AND ADMINISTRATION

- Adult Patients
  - Bolus: 10 microL/kg intravenously over 30 seconds to 60 seconds followed by a 10 mL flush of 0.9% Sodium Chloride Injection.
  - Infusion: 1.3 mL added to 50 mL of 0.9% Sodium Chloride Injection intravenously starting at 4 mL/minute, titrating as necessary, not to exceed 10 mL/minutes.
  - The maximum dose is two bolus doses 30 minute apart or one single infusion. (2.2)
- Pediatric Patients
  - Bolus: 3 microL/kg over 30 seconds to 60 seconds by intravenous bolus injection followed by a 5 mL flush of 0.9% Sodium Chloride Injection.
  - The maximum dose is two bolus doses 30 minute apart. (2.3)
- See Full Prescribing Information for imaging instructions and preparation. (2.4, 2.5)

3 DOSAGE FORMS AND STRENGTHS

DEFINITY: 6.52 mg/mL perflutren in the head space and 0.75 mg/mL of a lipid blend as liquid with 1.5 mL volume in a single-patient use vial; after activation, each mL contains a maximum of 1.2×10^10 perflutren lipid microspheres as injectable suspension (3)

4 CONTRAINDICATIONS

Known or suspected hypersensitivity to perflutren lipid microsphere or its components, such as polyethylene glycol (PEG). (4)

5 WARNINGS AND PRECAUTIONS

- Hypersensitivity Reactions: Serious acute hypersensitivity reactions have occurred. Always have cardiopulmonary resuscitation personnel and equipment readily available prior to DEFINITY administration and monitor all patients for acute reactions. (5.2)
- Pain Episodes in Patients with Sickle Cell Disease: Discontinue DEFINITY for new or worsening pain. (5.5)

6 ADVERSE REACTIONS

The most common adverse reactions (≥0.5%) are headache, back/renal pain, flushing, nausea, chest pain, injection site reactions, and dizziness. (6)

To report SUSPECTED ADVERSE REACTIONS, contact Lantheus Medical Imaging, Inc. at 1-800-362-2668 or FDA at 1-800-FDA-1088 or www.fda.gov/medwatch.

FULL PRESCRIBING INFORMATION

WARNING: SERIOUS CARDIOPULMONARY REACTIONS

Serious cardiopulmonary reactions, including fatalities, have occurred uncommonly during or following perflutren-containing microsphere administration. Most serious reactions occur within 30 minutes of administration.

- Assess all patients for the presence of any condition that precludes DEFINITY administration [see Contraindications (4)].
- Always have resuscitation equipment and trained personnel readily available [see Warnings and Precautions (5.1)] .

1 INDICATIONS AND USAGE

DEFINITY is indicated, after activation, for use in adult and pediatric patients with suboptimal echocardiograms to opacify the left ventricular chamber and to improve the delineation of the left ventricular endocardial border.

2 DOSAGE AND ADMINISTRATION

2.1 Important Preparation and Administration Instructions

- There are two formulations, DEFINITY and DEFINITY RT, that have differences in preparation and storage. Ensure of the correct product when following the directions for preparation and storage.
- DEFINITY must be activated using the VIALMIX or VIALMIX RFID device before administration according to the instructions outlined below [see Dosage and Administration (2.5)].
- DEFINITY is for intravenous use only and must not be administered by intra-arterial injection [see Warnings and Precautions (5.3)].
- For adult patients, DEFINITY can be administered by either an intravenous bolus or infusion. The maximum dose is either two bolus doses or one single infusion. Do not administer the bolus and infusion dosing in combination or in sequence [see Dosage and Administration (2.2)].
- For pediatric patients, DEFINITY is administered by an intravenous bolus injection only. The maximum dose is two bolus doses [see Dosage and Administration (2.3)].

2.2 Recommended Dosage in Adult Patients

Bolus Dosing

The recommended bolus dose in adult patients is 10 microL/kg of activated DEFINITY administered intravenously over 30 to 60 seconds followed by a 10 mL flush of 0.9% Sodium Chloride Injection, USP. If necessary, administer a second 10 microL/kg dose followed by a second 10 mL flush of 0.9% Sodium Chloride Injection, USP 30 minutes after the first injection to prolong contrast enhancement.

Infusion Dosing

The recommended infusion dose in adult patients is 1.3 mL of activated DEFINITY added to 50 mL of preservative-free 0.9% Sodium Chloride Injection, USP administered intravenously. Initiate infusion at 4 mL/minute, titrating the infusion rate as necessary to achieve optimal image enhancement, not to exceed 10 mL/minute.

2.3 Recommended Dosage in Pediatric Patients

Bolus Dosing

The recommended bolus dose in pediatric patients is 3 microL/kg of activated DEFINITY administered intravenously over 30 seconds to 60 seconds followed by a 5 mL flush of 0.9% Sodium Chloride Injection, USP. If necessary, administer a second bolus at a dose of 3 microL/kg to 5 microL/kg, followed by a second 5 mL flush of 0.9% Sodium Chloride Injection, USP 30 minutes after the first injection to prolong contrast enhancement.

2.4 Imaging Instructions

Adult Patients

After baseline non-contrast echocardiography is completed, set the mechanical index for the ultrasound device at 0.8 or below [see Warnings and Precautions (5.4)]. Then inject activated DEFINITY (as described above) and begin ultrasound imaging immediately [see Clinical Pharmacology(12.2). Evaluate the DEFINITY echocardiogram images in combination with the non-contrast echocardiogram images.

Pediatric Patients

After baseline non-contrast echocardiography is completed, set the mechanical index for the ultrasound transducer at 0.3 or below [see Warnings and Precautions (5.4)]. Then inject activated DEFINITY (as described above) and begin ultrasound imaging immediately [see Clinical Pharmacology(12.2). Evaluate the DEFINITY echocardiogram images in combination with the non-contrast echocardiogram images.

2.5 Instructions for Activation, Preparation, and Handling of DEFINITY

1. Adhere to strict aseptic procedures during preparation.
2. Allow the DEFINITY vial to warm to room temperature before starting the activation procedure.
3. Activate DEFINITY by shaking the vial for 45 seconds using a VIALMIX device or VIALMIX RFID device.
  Note: Use only the drug activated in a properly functioning VIALMIX or VIALMIX RFID for a full 45 second activation cycle. Do not reactivate the vial if VIALMIX or VIALMIX RFID did not properly activate the vial. Never reactivate a successfully activated DEFINITY vial (see step 4). Refer to the VIALMIX or VIALMIX RFID User's Guide for illustrations of the activation procedure and a properly functioning VIALMIX or VIALMIX RFID.
4. Activated DEFINITY appears as a homogeneous milky white suspension with a presence of foam/bubbles. Use immediately after activation. If the product is not used within 5 minutes of activation, resuspend the microspheres by 10 seconds of hand agitation by inverting the vial before the product is withdrawn in a syringe.
5. The activated DEFINITY may be used for up to 12 hours from the time of activation, but only after the microspheres are resuspended by hand agitation for 10 seconds. Store the activated DEFINITY at room temperature 20° to 25°C (68° to 77°F) in the original product vial.
6. Invert the vial and withdraw the activated homogeneous milky white suspension using the Intellipin (Dispensing Pin), the PINSYNC (Vented Vial Adapter 13mm), or 18 gauge to 20 gauge syringe needle from the middle of the liquid. Do not inject air into the DEFINITY Vial.
7. Use the product immediately after its withdrawal from the vial; do not allow the product to stand in the syringe.
8. For infusion dosing in adult patients, dilute 1.3 mL of activated DEFINITY in 50 mL of preservative-free 0.9% Sodium Chloride Injection, USP.
9. Parenteral drug products should be inspected visually for foreign particulate matter and discoloration prior to administration, whenever solution and container permit.

2.6 Instructions for RFID-Tagged Vials

The radio frequency identification (RFID) tag integrated on the back of the vial label when used with VIALMIX RFID allows for the exchange of product information such as activation time and activation rate. If the RFID tag is damaged or otherwise non-functional, the vial with the non-functional RFID tag cannot be activated with VIALMIX RFID. Discard the non-functional RFID-tagged vial. Do not activate RFID-tagged DEFINITY vials in the VIALMIX RFID within 6 inches (15 cm) of a pacemaker and/or defibrillator (see the VIALMIX RFID User's Guide).

3 DOSAGE FORMS AND STRENGTHS

DEFINITY is supplied in a single-patient use vial containing 6.52 mg/mL perflutren in the headspace and 0.75mg/mL of a lipid blend as a clear colorless liquid with 1.5 mL volume. After activation, each mL contains a maximum of 1.2 × 10^10 perflutren lipid microspheres as a homogeneous milky white injectable suspension, and about 150 microL/mL (1.1 mg/mL) perflutren.

4 CONTRAINDICATIONS

DEFINITY is contraindicated in patients with known or suspected hypersensitivity to perflutren lipid microsphere or its components, such as polyethylene glycol (PEG) [see Warnings and Precautions (5.2) and Description (11)].

5 WARNINGS AND PRECAUTIONS

5.1 Serious Cardiopulmonary Reactions

Serious cardiopulmonary reactions including fatalities have occurred uncommonly during or shortly following perflutren-containing microsphere administration, typically within 30 minutes of administration. The risk for these reactions may be increased among patients with unstable cardiopulmonary conditions (acute myocardial infarction, acute coronary artery syndromes, worsening or unstable congestive heart failure, or serious ventricular arrhythmias). Always have cardiopulmonary resuscitation personnel and equipment readily available prior to DEFINITY administration and monitor all patients for acute reactions.

The reported reactions include: fatal cardiac or respiratory arrest, shock, syncope, symptomatic arrhythmias (atrial fibrillation, tachycardia, bradycardia, supraventricular tachycardia, ventricular fibrillation, ventricular tachycardia), hypertension, hypotension, dyspnea, hypoxia, chest pain, respiratory distress, stridor, wheezing, loss of consciousness, and convulsions [see Adverse Reactions (6.2)].

5.2 Hypersensitivity Reactions

In postmarketing use, serious hypersensitivity reactions were observed during or shortly following perflutren-containing microsphere administration including:

Anaphylaxis, with manifestations that may include death, shock, bronchospasm, throat tightness, angioedema, edema (pharyngeal, palatal, mouth, peripheral, localized), swelling (face, eye, lip, tongue, upper airway), facial hypoesthesia, rash, urticaria, pruritus, flushing, and erythema.

These reactions have occurred in patients with no prior exposure to perflutren-containing microsphere products. DEFINITY contains PEG. There may be increased risk of serious reactions including death in patients with prior hypersensitivity reaction(s) to PEG [see Adverse Reactions (6.2) and Description (11)]. Clinically assess patients for prior hypersensitivity reactions to products containing PEG, such as certain colonoscopy bowel preparations and laxatives. DEFINITY is contraindicated in patients with known or suspected hypersensitivity to perflutren lipid microsphere or its components such as PEG [see Contraindications (4)]. Always have cardiopulmonary resuscitation personnel and equipment readily available prior to DEFINITY administration and monitor all patients for hypersensitivity reactions.

5.3 Systemic Embolization

When administering DEFINITY to patients with a cardiac shunt, the microspheres can bypass filtering by the lung and enter the arterial circulation. Assess patients with shunts for embolic phenomena following DEFINITY administration. DEFINITY is only for intravenous administration and must not be administered by intra-arterial injection [see Dosage and Administration (2.1,2.2,2.3)].

5.4 Ventricular Arrhythmia Related to High Mechanical Index

High ultrasound mechanical index values may cause microsphere cavitation or rupture and lead to ventricular arrhythmias. Additionally, end-systolic triggering with high mechanical indices has been reported to cause ventricular arrhythmias. The maximum recommended mechanical index for use with DEFINITY is 0.8 in adult patients and 0.3 in pediatric patients [see Dosage and Administration (2.4)].

5.5 Pain Episodes in Patients with Sickle Cell Disease

In postmarketing reports, acute pain episodes shortly following DEFINITY administration have been reported in patients with sickle cell disease (SCD). The pain episodes included moderate to severe back pain and vaso-occlusive crisis [see Adverse Reactions (6.2)]. If a patient with sickle cell disease experiences new or worsening pain, discontinue DEFINITY.

6 ADVERSE REACTIONS

The following serious adverse reactions are described elsewhere in the labeling:

- Serious Cardiopulmonary Reactions [see Warnings and Precautions (5.1)]
- Hypersensitivity Reactions [see Warnings and Precautions(5.2)]
- Pain Episodes in Patients with Sickle Cell Disease [see Warnings and Precautions (5.5)]

6.1 Clinical Trials Experience

Because clinical trials are conducted under widely varying conditions, adverse reaction rates observed in the clinical trials of a drug cannot be directly compared to rates in the clinical trials of another drug and may not reflect the rates observed in practice.

Adverse Reactions in Adults

Safety of DEFINITY was evaluated in a total of 1,716 adult subjects in pre-market clinical trials. In this group, 1,063 (62%) were male and 653 (38%) were female, 1,328 (77%) were White, 258 (15%) were Black or African American, 74 (4%) were Hispanic, and 56 (3%) were classified as other racial or ethnic groups. The mean age was 56 years (range 18 to 93).

Among the 1,716 subjects, 19 (1.1%) suffered serious cardiopulmonary adverse reactions.

Adverse reactions that led to discontinuation in a total of 15 (0.9%) subjects receiving DEFINITY in the clinical trials included urticaria, pruritus, dizziness, chest pain, dyspnea, and back pain.

Table 1 summarizes the most common adverse reactions occurring at ≥0.5%.

Table 1 Adverse Reactions Occurring in ≥0.5% of All DEFINITY-Treated Subjects
 | DEFINITY (N=1716)
Total Number of Adverse Reactions | 269
Total Number of Subjects with an Adverse Reaction | 144 | (8.4%)
Body system
Preferred term | n | (%)
Application Site Disorders | 11 | (0.6)
Injection Site Reactions | 11 | (0.6)
Body as a Whole | 41 | (2.4)
Back/renal pain | 20 | (1.2)
Chest pain | 13 | (0.8)
Central and peripheral nervous system disorder | 54 | (3.1)
Headache | 40 | (2.3)
Dizziness | 11 | (0.6)
Gastrointestinal system | 31 | (1.8)
Nausea | 17 | (1.0)
Vascular (extracardiac) disorders | 19 | (1.1)
Flushing | 19 | (1.1)
N=Sample size 1716 subjects who received activated DEFINITY
n=Number of subjects reporting at least one Adverse Reaction

Other adverse reactions that occurred in ≤0.5% of the activated DEFINITY-dosed subjects were:

Body as a Whole: Fatigue, fever, hot flushes, pain, rigors, and syncope

Cardiovascular: Abnormal ECGs, bradycardia, tachycardia, palpitation, hypertension and hypotension

Digestive: Dyspepsia, dry mouth, tongue disorder, toothache, abdominal pain, diarrhea and vomiting

Hematology: Granulocytosis, leukocytosis, leukopenia, and eosinophilia

Musculoskeletal: Arthralgia

Nervous System: Leg cramps, hypertonia, vertigo and paresthesia

Platelet, Bleeding, and Clotting: Hematoma

Respiratory: Coughing, hypoxia, pharyngitis, rhinitis and dyspnea

Special Senses: Decreased hearing, conjunctivitis, abnormal vision and taste perversion

Skin: Pruritus, rash, erythematous rash, urticaria, increased sweating, and dry skin

Urinary: Albuminuria

Adverse Reactions in Pediatric Patients

In a study of DEFINITY in 40 pediatric patients 1 month of age and older, no new safety signals were observed [see Use in Specific Populations (8.4) and Clinical Pharmacology (12.2)].

In published studies of DEFINITY in 149 patients 5 years to 24 years of age (mean age 16.8 years; 56% male) clinically indicated for echocardiography, no additional safety signals were observed.

6.2 Postmarketing Experience

Adverse Reactions from Observational Studies

In a prospective, multicenter, open-label registry of 1,053 patients receiving DEFINITY in routine clinical practice, heart rate, respiratory rate, and pulse oximetry were monitored for 30 minutes after DEFINITY administration. No deaths or serious adverse reactions were reported.

Adverse Reactions from Postmarketing Spontaneous Reports

The following adverse reactions have been identified during the post-marketing use of perflutren and PEG-containing microsphere products. Because these reactions are reported voluntarily from a population of uncertain size, it is not always possible to reliably estimate their frequency or establish a causal relationship to drug exposure.

Cardiopulmonary

Fatal cardiac or respiratory arrest, shock, syncope, symptomatic arrhythmias (atrial fibrillation, tachycardia, bradycardia, supraventricular tachycardia, ventricular fibrillation, ventricular tachycardia), hypertension, hypotension, dyspnea, hypoxia, chest pain, respiratory distress, stridor, wheezing.

Immune System

Anaphylaxis, with manifestations that may include death, shock, bronchospasm, throat tightness, angioedema, edema (pharyngeal, palatal, mouth, peripheral, localized), swelling (face, eye, lip, tongue, upper airway), facial hypoesthesia, rash, urticaria, pruritus, flushing, and erythema.

Neurologic

Coma, loss of consciousness, convulsion, seizure, transient ischemic attack, agitation, tremor, vision blurred, dizziness, headache, fatigue.

Blood and Lymphatic System

Acute pain episodes including vaso-occlusive crisis in patients with sickle cell disease.

8 USE IN SPECIFIC POPULATIONS

8.1 Pregnancy

Risk Summary

Available data from case reports with DEFINITY use in pregnant women have not identified a drug-associated risk of major birth defects, miscarriage, or adverse maternal or fetal outcomes. DEFINITY has a very short half-life; therefore, administration of DEFINITY to a pregnant woman is not expected to result in clinically relevant fetal exposure. No adverse developmental outcomes were observed in animal reproduction studies with administration of activated DEFINITY in pregnant rats and rabbits during organogenesis at doses up to 8 and 16 times, respectively, the maximum human dose based on body surface area (see Data).

All pregnancies have a background risk of birth defects, loss, or other adverse outcomes. In the U.S. general population, the estimated background risk of major birth defects and miscarriage in clinically recognized pregnancies is 2% to 4% and 15% to 20%, respectively.

Data

Animal Data

DEFINITY was administered intravenously to rats at doses of 0.1 mL/kg, 0.3 mL/kg, and 1 mL/kg (approximately 0.8, 2.4, and 8 times the recommended maximum human dose based on body surface area); DEFINITY doses were administered daily from day 6 to day 17 of gestation. DEFINITY was administered intravenously to rabbits at doses of 0.1mL/kg, 0.3 mL/kg, and 1 mL/kg (approximately, 1.6, 4.8, and 16 times the recommended maximum human dose based on body surface area); DEFINITY doses were administered daily from day 7 to day 19 of gestation. No significant findings on the fetus were observed.

8.2 Lactation

Risk Summary

There are no data on the presence of perflutren lipid microspheres in human milk, the effects on the breastfed infant, or the effects on milk production. The developmental and health benefits of breastfeeding should be considered along with the mother's clinical need for DEFINITY and any potential adverse effects on the breastfed infant from DEFINITY or from the underlying maternal condition.

8.4 Pediatric Use

The safety and effectiveness of DEFINITY have been established for use in pediatric patients with suboptimal echocardiograms to opacify the left ventricular chamber and to improve delineation of the left endocardial border. Use of DEFINITY for this indication is supported by evidence from adequate and well-controlled studies in adults [see Clinical Studies (14)], a pharmacodynamic and safety study in 40 pediatric patients 1 month of age and older [see Adverse Reactions (6.1) and Clinical Pharmacology (12.2)], and published studies in 149 patients 5 years to 24 years of age [see Adverse Reactions (6.1)].

8.5 Geriatric Use

Of the total number of subjects in clinical trials of DEFINITY, 144 (33%) were 65 and over. No overall differences in safety or effectiveness were observed between these subjects and younger subjects, and other reported clinical experience has not identified differences between the elderly and younger patients.

11 DESCRIPTION

DEFINITY (perflutren lipid microsphere) injectable suspension is, after activation an ultrasound contrast agent for intravenous use.

The perflutren lipid microspheres are composed of perflutren encapsulated in an outer lipid shell consisting of (R) – hexadecanoic acid, 1-[(phosphonoxy)methyl]-1,2-ethanediyl ester, monosodium salt (abbreviated DPPA); (R) - 4-hydroxy-N,N,N-trimethyl-10-oxo-7-[(1-oxohexadecyl)oxy]-3,4,9-trioxa-4-phosphapentacosan-1-aminium, 4-oxide, inner salt (abbreviated DPPC); and (R)-∝-[6-hydroxy-6-oxido-9-[(1-oxohexadecyl)oxy]-5,7,11-trioxa-2-aza-6-phosphahexacos-1-yl]- ω-methoxypoly(ox-1,2-ethanediyl), monosodium salt; commonly called N-(methoxypolyethylene glycol 5000 carbamoyl)-1,2-dipalmitoyl-sn-glycero-3- phosphatidylethanolamine, monosodium salt (abbreviated MPEG5000 DPPE).

Perflutren is chemically characterized as 1,1,1,2,2,3,3,3-octafluoropropane. It has a molecular weight of 188, empirical formula of C3F8 and has the following structural formula:

DPPA has a molecular weight of 670, empirical formula of C35H68O8PNa, and following structural formula:

DPPC has a molecular weight of 734, empirical formula of C40H80NO8P, and following structural formula:

MPEG5000 DPPE has an approximate molecular weight of 5750 represented by empirical formula C265H527NO123PNa, contains <100ppm Ca^2+ and Mg^2+ and the following structural formula:

Prior to activation, perflutren is in the headspace of the vial with a concentration of 6.52 mg/mL which is confirmed by positive IR spectroscopic testing in every vial. The lipid blend is in the clear, colorless, hypertonic, sterile liquid. Each mL of the liquid contains 0.75 mg lipid blend (consisting of 0.045 mg DPPA, 0.401 mg DPPC, and 0.304 mg MPEG5000 DPPE) and the following inactive ingredients: 103.5 mg propylene glycol, 126.2 mg glycerin, 2.34 mg sodium phosphate monobasic monohydrate, 2.16 mg sodium phosphate dibasic heptahydrate, and 4.87 mg sodium chloride in water for injection. The pH is 6.2 to 6.8. DEFINITY does not contain bacterial preservative.

After activation with the aid of the VIALMIX or VIALMIX RFID, each mL of the activated DEFINITY as homogenous milky white suspension contains a maximum of 1.2 × 10^10 perflutren lipid microspheres, and about 150 microL/mL (1.1 mg/mL) perflutren. The microsphere particle size parameters are listed in Table 2 below:

Table 2 Microsphere Size Distribution
 | Microsphere particle size parameters
Mean diameter range | 1.1 µm – 3.3 µm
Percent less than 10 µm | 98%
Maximum diameter | 20 µm

12 CLINICAL PHARMACOLOGY

12.1 Mechanism of Action

Perflutren lipid microspheres exhibit lower acoustic impedance than blood and enhance the intrinsic backscatter of blood. These physical acoustic properties of activated DEFINITY provide contrast enhancement of the left ventricular chamber and aid delineation of the left ventricular endocardial border during echocardiography.

In animal models the acoustic properties of activated DEFINITY were established at or below a mechanical index of 0.7 (1.8 MHz frequency). In clinical trials, the majority of the patients were imaged at or below a mechanical index of 0.8.

12.2 Pharmacodynamics

Contrast Enhancement Duration in Adults

In a crossover trial of 64 adult subjects randomized to both bolus and infusion, the duration of clinically useful contrast enhancement for fundamental imaging was approximately 3.4 minutes after a 10 microL/kg bolus and was approximately 7.1 minutes during the continuous infusion of 1.3 mL activated DEFINITY in 50 mL saline at a rate of 4 mL/min.

Dose-Ranging and Contrast Enhancement Duration in Pediatric Patients

In a pharmacodynamic and safety study, DEFINITY was administered to 40 pediatric patients 1 month of age and older clinically indicated for echocardiography (60% male; 10 patients were 1 month to younger than 1 year of age; 9 patients were 1 to 5 years of age; 10 patients were 6 to 10 years of age; 10 patients were 11 to 16 years of age; and 1 patient was 17 years of age). Patients underwent echocardiography with a mechanical index of ≤ 0.3 and received DEFINITY as a series of sequential bolus injections (3 microL/kg and 5 microL/kg) with each injection separated by approximately 7 minutes. Patients had acceptable cardiac imaging at baseline. Left ventricular opacification with DEFINITY was graded as adequate or full in 80% to 95% of patients (depending on view) at the 3 microL/kg dose and 85% to 88% of patients at the 5 microL/kg dose [see Dosage and Administration (2.3)]. The mean duration of clinically useful contrast enhancement was approximately 2.7 minutes after a bolus dose of 3 microL/kg and 3.9 minutes after a bolus dose of 5 microL/kg.

Pulmonary Hemodynamic Effects

The impact of DEFINITY on pulmonary hemodynamics was explored in a prospective, open-label study of patients with normal (≤ 35 mmHg, 16 patients) and elevated (> 35 mmHg, ≤ 75 mmHg, 16 patients) pulmonary artery systolic pressure undergoing right heart catheterization. Patients with pulmonary artery systolic pressure greater than 75 mmHg were excluded from this study. Systemic hemodynamic parameters and ECGs were also evaluated. No clinically important pulmonary hemodynamic, systemic hemodynamic, or ECG changes were observed.

12.3 Pharmacokinetics

Human pharmacokinetics information is not available for the intact or degassed lipid microspheres. The pharmacokinetics of perflutren gas was evaluated in healthy subjects (n=8) after the intravenous administration of activated DEFINITY at 50 microL/kg (5 times the recommended dose).

Distribution

Perflutren gas binding to plasma proteins or partitioning into blood cells has not been studied. However, perflutren protein binding is expected to be minimal due to its low partition coefficient into whole blood.

Elimination

Metabolism

Perflutren is a stable gas that is not metabolized. The phospholipid components of the microspheres are thought to be metabolized to free fatty acids.

Excretion

Perflutren was not detectable after 10 minutes in most subjects either in the blood or in expired air. Perflutren concentrations in blood were shown to decline in a mono-exponential fashion with a mean half-life of 1.3 minutes in healthy subjects.

Specific Populations

Patients with Obstructive Pulmonary Disease

The pharmacokinetics of perflutren gas was evaluated in subjects (n=11) with chronic obstructive pulmonary disease (COPD). The mean half-life of perflutren in blood was 1.9 minutes. The total lung clearance of perflutren was similar to that in healthy subjects.

13 NONCLINICAL TOXICOLOGY

13.1 Carcinogenesis, Mutagenesis, and Impairment of Fertility

Studies with activated DEFINITY have not been performed to evaluate carcinogenic potential. Evidence of genotoxicity was not found in the following studies with activated DEFINITY: 1) bacterial mutagenesis assay (Ames assay), 2) in vitro mammalian mutagenesis assay, 3) in vitro human lymphocyte chromosome aberration assay, and 4) in vivo rat micronucleus assay.

Impairment of male or female fertility was not observed in rats and rabbits treated with activated DEFINITY at doses up to 24 and 15 times the human dose based on body surface area (in rats and rabbits respectively).

14 CLINICAL STUDIES

Effectiveness and safety of DEFINITY were evaluated in four controlled clinical trials (two open-label baseline controlled, unpaired blinded image evaluation studies and two identical placebo-controlled, unpaired blinded image evaluation studies) in 249 subjects who had two or more (of six) non-evaluable segments in either the apical 2- or 4-chamber view in non-contrast fundamental echocardiography.

In this group, 154 (62%) were male and 95 (38%) were female; 183 (74%) were White, 38 (15%) were Black or African American, 21 (8%) were Hispanic, and 7 (3%) were classified as other racial or ethnic groups. The mean age was 54 years (range 18 to 87).

In the two open-label baseline controlled studies, a total of 126 (67 in study A and 59 in study B) subjects received a bolus dose of 10 microL/kg activated DEFINITY. The outcome measures in these studies included the blinded assessment of ejection fraction (EF), endocardial border length (EBL) obtained by direct measurement, and qualitative assessment of wall motion.

In the two placebo-controlled studies a total of 123 subjects were randomized in 1:2 ratio to receive two intravenous bolus doses of either 0.9% Sodium Chloride Injection (placebo) or activated DEFINITY 10 microL/kg (17 placebo vs. 33 DEFINITY subjects and 24 placebo vs. 49 DEFINITY subjects, respectively). The outcome measure for assessing the effectiveness of DEFINITY was the blinded assessment of improvement in ventricular chamber enhancement (measured by videodensitometry at end-diastole and end-systole).

Endocardial Border Length

As shown in Table 3, compared to baseline, a single bolus dose of 10 microL/kg of activated DEFINITY increased the length of endocardial border that could be measured at both end-systole and end-diastole. The mean change in border length from baseline at end-diastole was statistically significant for all readers in the apical 4-chamber view and for 3 out of 4 readers for the apical 2-chamber view. The mean change in border length from baseline at end-systole was statistically significant for 3 out of 4 readers for the apical 4-chamber view and for 2 out of 4 readers for the apical 2-chamber view.

Ventricular Chamber Enhancement

Left ventricular chamber enhancement after an activated DEFINITY dose of 10 microL/kg was significantly increased from baseline compared to placebo in both views at the mid-ventricular and apical levels at end-diastole. Similar results were noted at end-systole, with the exception of the 4-chamber view.

Wall Motion

In a retrospective analysis, in a subset of subjects (n=12 to 47, depending on reader) having at least 2 adjacent segments non-evaluable on non-contrast imaging, DEFINITY converted a baseline non-evaluable image to an evaluable image in 58 to 91% of the subjects, depending on the reader. In the converted images, the accuracy of wall motion (i.e., normal versus abnormal) improved in 42 to 71% of the subjects, depending on the reader, however, improvement in the specific diagnostic accuracy (e.g., hypokinetic, akinetic etc.) was not established. Also, in 13 to 37% of the subjects, depending on the reader, DEFINITY was found to obscure the wall motion rendering the image non-evaluable.

Ejection Fraction

In the 2 baseline controlled studies, ejection fraction results were evaluated in comparison to MRI. The results were evaluated by 3 blinded, independent radiologists. In these studies, although there was a statistically significant increase in ventricular chamber enhancement, DEFINITY did not significantly improve the assessment of ejection fraction compared to the baseline images.

Table 3 MEAN (SD) ENDOCARDIAL BORDER LENGTH (CM) BY BOTH APICAL 2- AND 4-CHAMBER VIEWS AT END-SYSTOLE AND END-DIASTOLE BY STUDY, EVALUABLE SUBJECTS
Study/View | Endocardial Border Length – Blinded Read
Study/View | Mean(SD) at End-Diastole |  | Mean(SD) at End-Systole
Study/View | Reader 1 | Reader 2 | Reader 1 | Reader 2
Study A: (N = 67)
Apical 2-chamber
Baseline | 8.0(3.4) | 4.7(2.8) | 7.1(3.3) | 4.3(2.6)
Post-DEFINITY | 12.8(5.2) [Significant change from baseline (paired t-test, p<0.05)] | 5.8(2.6) | 10.6(5.0) | 4.4(2.3)
Apical 4-chamber
Baseline | 8.1(3.3) | 4.5(2.6) | 7.6(3.2) | 4.5(2.7)
Post-DEFINITY | 13.5(5.2) | 6.8(3.3) | 11.5(4.4) | 5.3(3.1)
Study B: (N = 59)
Apical 2-chamber
Baseline | 4.3(2.6) | 7.8(5.3) | 4.1(2.4) | 6.5(5.1)
Post-DEFINITY | 5.7(4.7) | 8.2(6.5) | 5.5(4.4) | 6.9(6.3)
Apical 4-chamber
Baseline | 4.0(2.7) | 9.2(5.9) | 3.8(2.6) | 7.3(5.6)
Post-DEFINITY | 7.1(5.5) | 11.5(7.5) | 5.9(5.3) | 8.7(6.3)
Activated DEFINITY Bolus Dose = 10 µL/kg

16 HOW SUPPLIED/STORAGE AND HANDLING

How Supplied

DEFINITY (perflutren lipid microsphere) injectable suspension is supplied in a single- patient use clear glass vial or a single patient use clear glass Radio Frequency Identification (RFID)-tagged vial containing 6.52 mg/mL perflutren in the headspace of the vial and 0.75 mg/mL of a lipid blend in a clear, colorless liquid phase with 1.5 mL volume. DEFINITY is available in the following packages:

- One (1) vial or RFID-tagged vial per carton NDC (11994-011-01)
- Four (4) vials or RFID-tagged vials per carton - NDC (11994-011-04)
- Sixteen (16) vials or RFID-tagged vials per carton - NDC (11994-011-16)

Order VIALMIX or VIALMIX RFID from Lantheus Medical Imaging.

Storage and Handling

Before activation store between 2° to 8°C (36° to 46°F).

Regarding interference with medical devices, the RFID tag and VIALMIX RFID unit meets the IEC 60601-1-2 requirements for emission and immunity standards for medical devices.

17 PATIENT COUNSELING INFORMATION

Hypersensitivity Reactions

Advise patients to inform their healthcare provider if they develop any symptoms of hypersensitivity after DEFINITY administration, including rash, wheezing, or shortness of breath [see Warnings and Precautions (5.2)].

Distributed By
Lantheus Medical Imaging
331 Treble Cove Road
N. Billerica, Massachusetts 01862 USA
For ordering, call toll free: 800-299-3431
All Other Business: 800-362-2668
(For Massachusetts and International, call 978-667-9531)
Patent: http://www.lantheus.com/patents/index.html

515987-0324

PACKAGE LABEL

PRINCIPAL DISPLAY PANEL - 2 mL Vial Carton

DEFINITY®
VIAL
FOR
(Perflutren Lipid Microsphere)
INJECTABLE SUSPENSION

NDC 11994-011-16
Sterile

CAUTION: Rx Only

16x2 mL Single-Dose Containers
Non-Pyrogenic

For Intravenous Use Only, After Activation
Store refrigerated, 2° to 8° C (36° to 46° F)
For Single Use Only, Discard Unused Portion
Use within 12 hours of activation (see Insert)
IMPORTANT: Read enclosed Package Insert for full information on preparation, use and indications.
CONTAINS NO BACTERIOSTATIC PRESERVATIVE

Lantheus
Medical Imaging